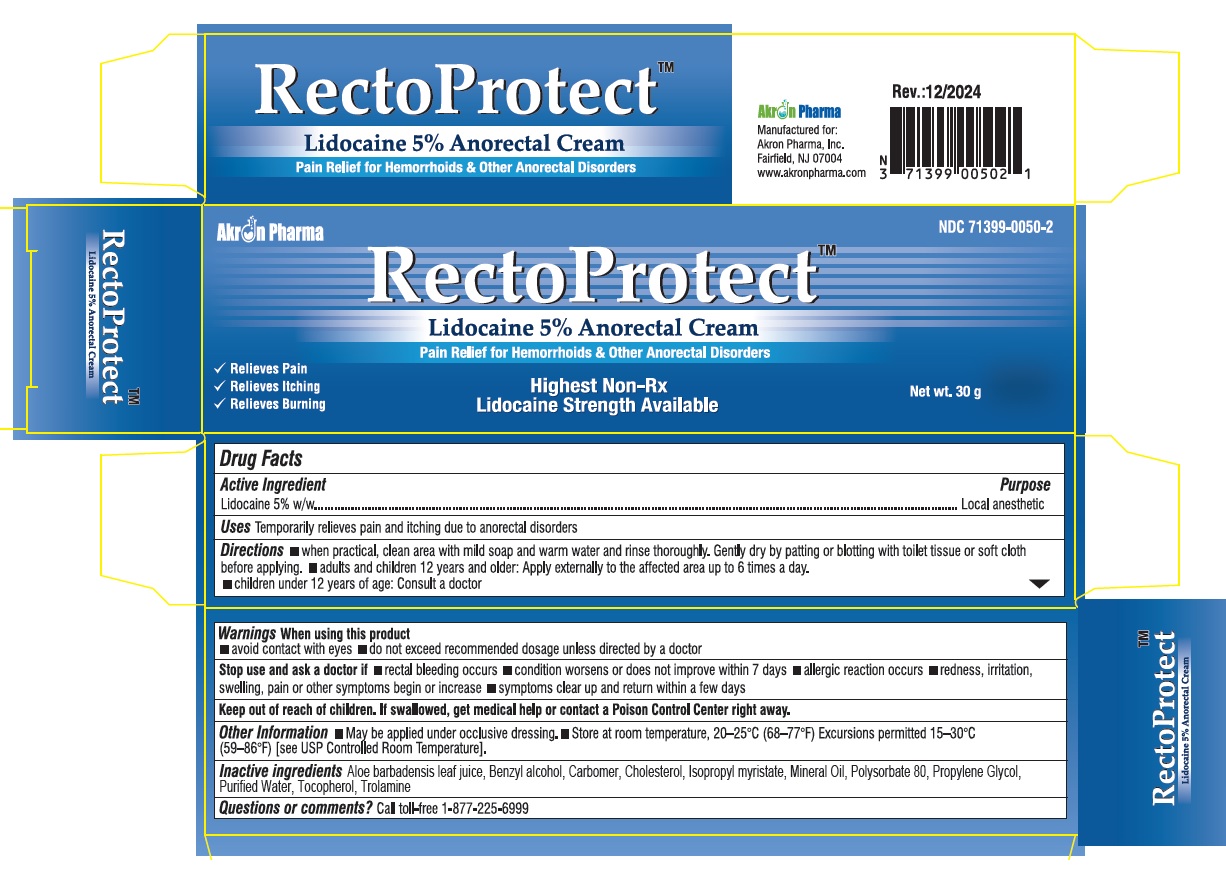 DRUG LABEL: RectoProtect
NDC: 71399-0050 | Form: CREAM
Manufacturer: Akron Pharma Inc.
Category: otc | Type: HUMAN OTC DRUG LABEL
Date: 20250119

ACTIVE INGREDIENTS: LIDOCAINE 5 g/100 g
INACTIVE INGREDIENTS: ALOE BARBADENSIS LEAF JUICE; BENZYL ALCOHOL; CARBOMER; CHOLESTEROL; ISOPROPYL MYRISTATE; MINERAL OIL; POLYSORBATE 80; PROPYLENE GLYCOL; WATER; TOCOPHEROL; TROLAMINE

RectoProtect (Lidocaine 5% Anorectal Cream)
Pain Relief for Hemorrhoids & Other Anorectal Disorders

Active ingredient

Lidocaine 5% w/w

Purpose

Local anesthetic

Uses

Temporarily relieves pain and itching due to anorectal disorders

Directions

- when practical, clean area with mild soap and warm water and rinse thoroughly. Gently dry by patting or blotting with toilet tissue or soft cloth
- before applying.
- adults and children 12 years and older: Apply externally to the affected area up to 6 times a day.
- children under 12 years of age: Consult a doctor

Warnings

When using this product

- avoid contact with eyes
- do not exceed recommended dosage unless directed by a doctor

Stop use and ask a doctor if

- rectal bleeding occurs
- condition worsens or does not improve within 7 days
- allergic reaction occurs
- redness, irritation, swelling, pain or other symptoms begin or increase
- symptoms clear up and return within a few days

Other information

- May be applied under occlusive dressing.
- Store at room temperature, 20–25°C (68–77°F) Excursions permitted 15–30°C (59–86°F) [see USP Controlled Room Temperature].

Inactive ingredients

Aloe barbadensis leaf juice, Benzyl alcohol, Carbomer, Cholesterol, Isopropyl myristate, Mineral Oil, Polysorbate 80, Propylene Glycol, Purified Water, Tocopherol, Trolamine

Questions or comments?

Call toll-free 1-877-255-6999

Manufactured for:

Akron Pharma Inc.

Fairfield, Nj 07004

www.akronpharma.com